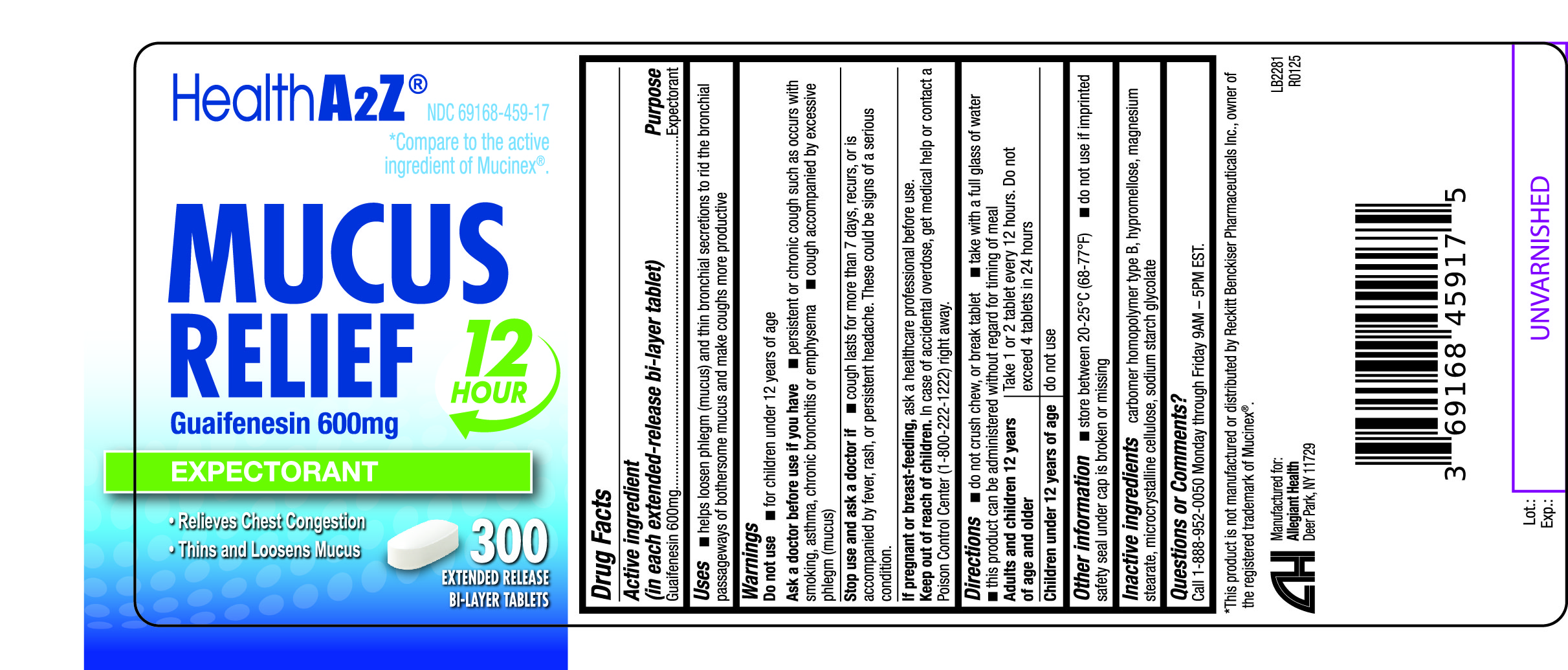 DRUG LABEL: Mucus Relief
NDC: 69168-459 | Form: TABLET, EXTENDED RELEASE
Manufacturer: Allegiant Health
Category: otc | Type: HUMAN OTC DRUG LABEL
Date: 20240424

ACTIVE INGREDIENTS: GUAIFENESIN 600 mg/1 1
INACTIVE INGREDIENTS: CARBOMER HOMOPOLYMER TYPE B (ALLYL PENTAERYTHRITOL OR ALLYL SUCROSE CROSSLINKED); HYPROMELLOSE 2910 (5 MPA.S); SODIUM STARCH GLYCOLATE TYPE A; MAGNESIUM STEARATE; MICROCRYSTALLINE CELLULOSE

459 - Mucus Relief

Active ingredient(s)

Guaifenesin 600 mg

Purpose

Expectorant

Use(s)

- helps loosen phlegm (mucus) and thin bronchial secretions to rid the bronchial passageways of bothersome mucus and make coughs more productive

Warnings

Do not use

- for children under 12 years of age

Ask a doctor before use if

- persistent or chronic cough such as occurs with smoking, asthma, chronic bronchitis, or emphysema
- cough accompanied by too much phlegm (mucus)

Stop use and ask a doctor if

- cough lasts more than 7 days, comes back, or occurs with fever, rash, or persistent headache. These could be signs of a serious illness.

If pregnant or breastfeeding,

ask a health professional before use.

Keep out of reach of children

In case of overdose, get medical help or contact a Poison Control Center right away
(1-800-222-1222)

Directions

- do not crush, chew, or break tablet
- take with a full glass of water
- this product can be administered without regard for timing of meals
- adults and children 12 years of age and over: 1 or 2 tablets every 12 hours. Do not exceed 4 tablets in 24 hours
- children under 12 years of age: do not use

Other information

- store between 20-25°C (68-77°F)
- do not use if imprinted safety seal under cap is broken or missing

Inactive ingredients

carbomer homopolymer type B; hypromellose, magnesium stearate, microcrystalline cellulose, sodium starch glycolate

Questions/Comments

Call 1-888-952-0050 Monday through Friday 9AM – 5PM EST.

Principal Display Panel

Mucus Relief